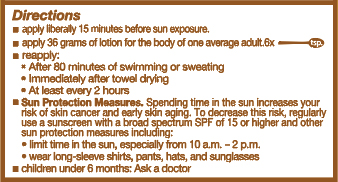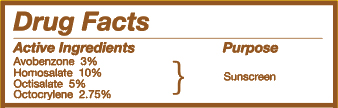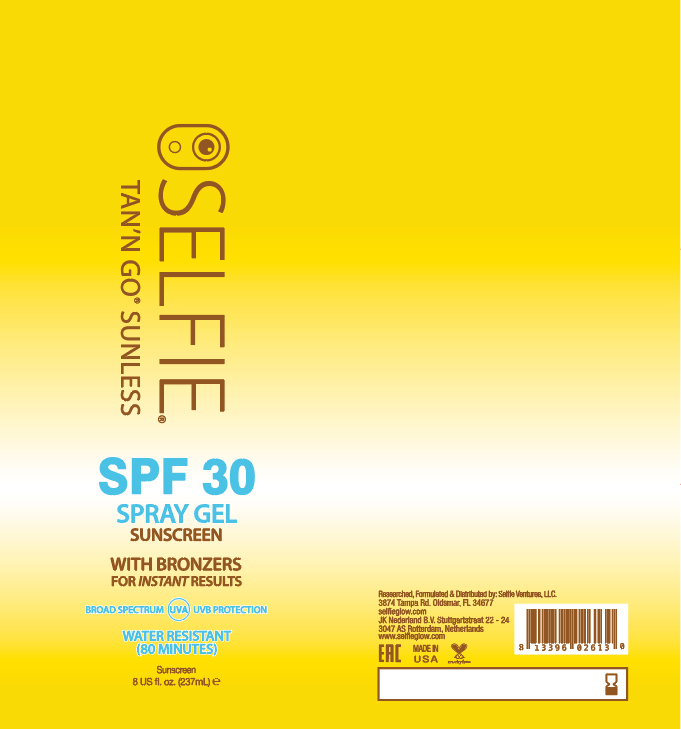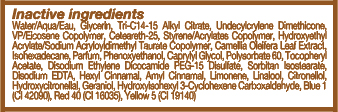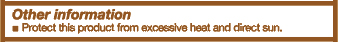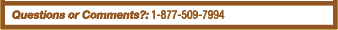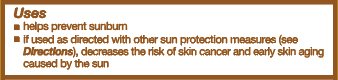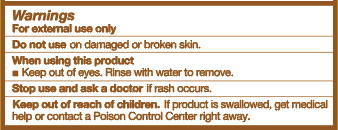 DRUG LABEL: Sunscreen
NDC: 72239-002 | Form: SPRAY
Manufacturer: O.L. Products, Inc,
Category: otc | Type: HUMAN OTC DRUG LABEL
Date: 20201231

ACTIVE INGREDIENTS: HOMOSALATE 3.61 g/36 g; OCTOCRYLENE 0.98 g/36 g; OCTISALATE 1.83 g/36 g; AVOBENZONE 1.1 g/36 g
INACTIVE INGREDIENTS: GLYCERIN

SPF 30 SELFIE